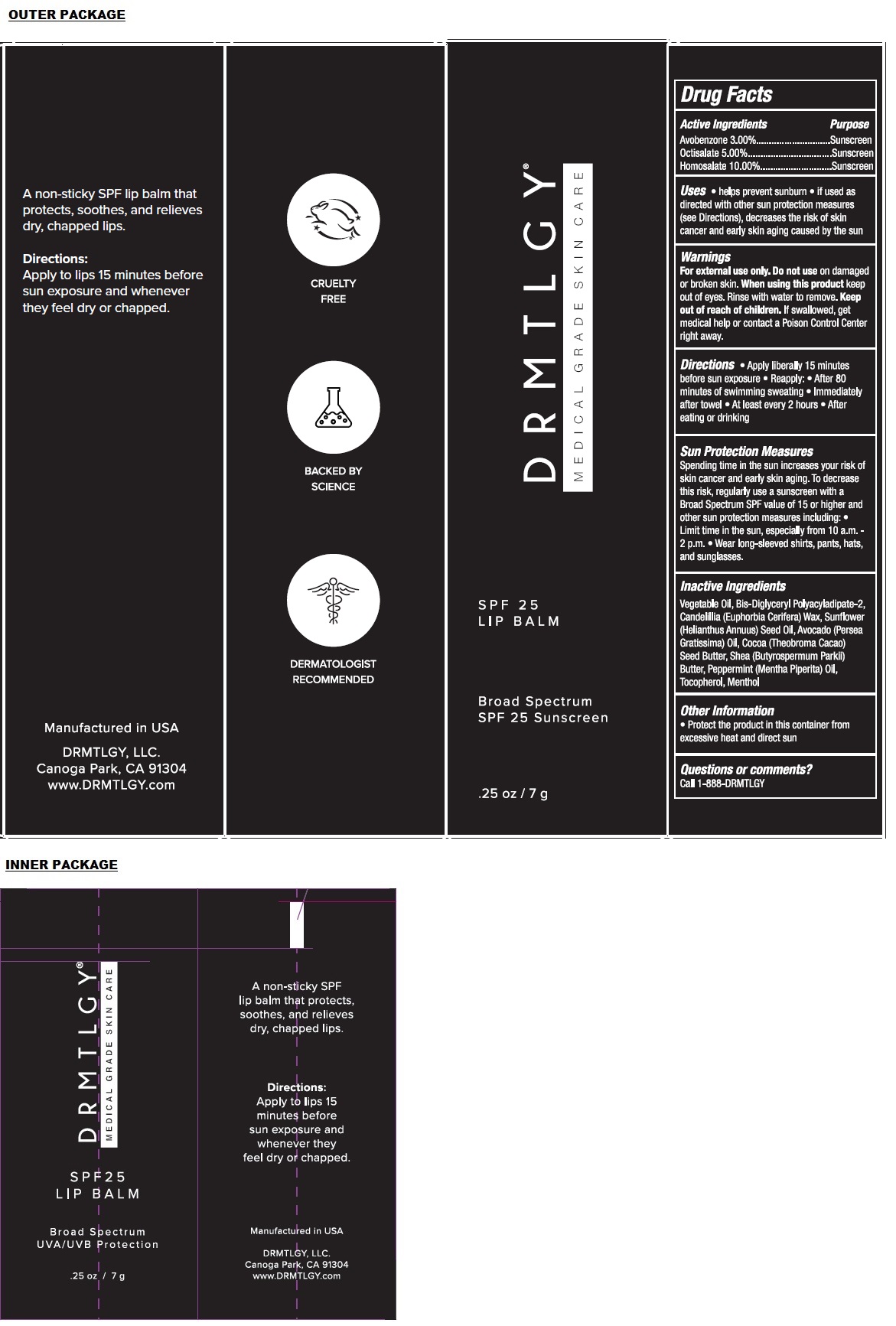 DRUG LABEL: SPF 25 LIP BALM
NDC: 83286-002 | Form: PASTE
Manufacturer: Drmtlgy, LLC
Category: otc | Type: HUMAN OTC DRUG LABEL
Date: 20251118

ACTIVE INGREDIENTS: AVOBENZONE 3 g/100 g; OCTISALATE 5 g/100 g; HOMOSALATE 10 g/100 g
INACTIVE INGREDIENTS: CASTOR OIL; BIS-DIGLYCERYL POLYACYLADIPATE-2; CANDELILLA WAX; SUNFLOWER OIL; AVOCADO OIL; COCOA BUTTER; SHEA BUTTER; PEPPERMINT OIL; TOCOPHEROL; MENTHOL, UNSPECIFIED FORM

DRMTLGY® SPF 25 LIP BALM

Active Ingredients

Avobenzone 3.00%
Octisalate 5.00%
Homosalate 10.00%

Purpose

Sunscreen

Uses

• helps prevent sunburn • if used as directed with other sun protection measures (see Directions), decreases the risk of skin cancer and early skin aging caused by the sun

Warnings

For external use only. Do not use on damaged or broken skin. When using this product keep out of eyes. Rinse with water to remove.

Keep out of reach of children. If swallowed, get medical help or contact a Poison Control Center right away.

Directions

• Apply liberally 15 minutes before sun exposure • Reapply: • After 80 minutes of swimming sweating • Immediately after towel • At least every 2 hours • After eating or drinking

Sun Protection Measures
Spending time in the sun increases your risk of skin cancer and early skin aging. To decrease this risk, regularly use a sunscreen with a Broad Spectrum SPF value of 15 or higher and other sun protection measures including: • Limit time in the sun, especially from 10 a.m. - 2 p.m. • Wear long-sleeved shirts, pants, hats, and sunglasses.

Inactive Ingredients

Vegetable Oil, Bis-Diglyceryl Polyacyladipate-2, Candelillia (Euphorbia Cerifera) Wax, Sunflower (Helianthus Annuus) Seed Oil, Avocado (Persea Gratissima) Oil, Cocoa (Theobroma Cacao) Seed Butter, Shea (Butyrospermum Parkii) Butter, Peppermint (Mentha Piperita) Oil, Tocopherol, Menthol

Other Information

• Protect the product in this container from excessive heat and direct sun

Questions or comments?

Call 1-888-DRMTLGY

MEDICAL GRADE SKIN CARE

Broad Spectrum SPF 25 Sunscreen

A non-sticky SPF lip balm that protects, soothes, and relieves dry, chapped lips.

Manufactured in USA

DRMTLGY, LLC.
Canoga Park, CA 91304
www.DRMTLGY.com

CRUELTY FREE

BACKED BY SCIENCE

DERMATOLOGIST RECOMMENDED